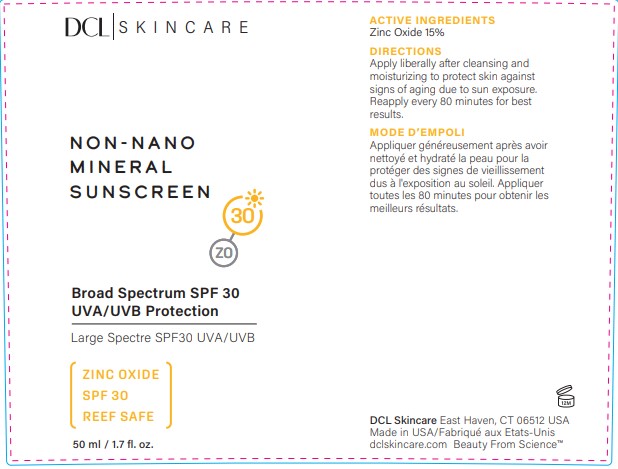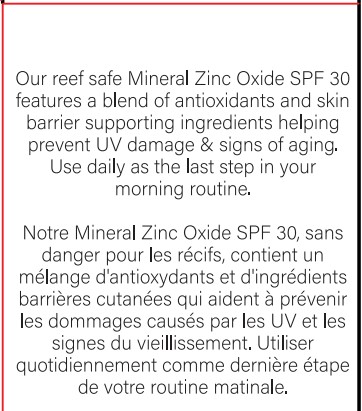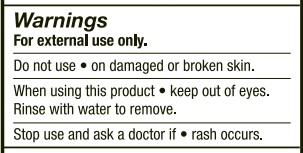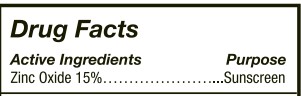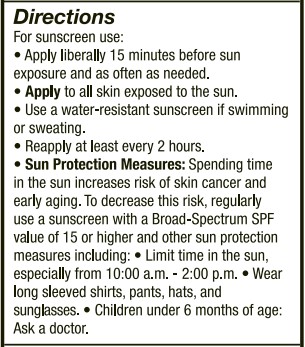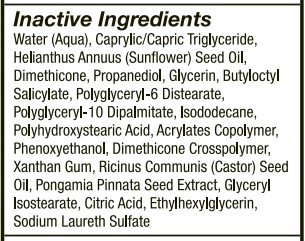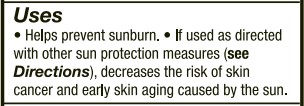 DRUG LABEL: Non nano mineral SPF30
NDC: 57577-821 | Form: LOTION
Manufacturer: Milbar Laboratories
Category: otc | Type: HUMAN OTC DRUG LABEL
Date: 20240724

ACTIVE INGREDIENTS: ZINC OXIDE 9.84 g/50 mL
INACTIVE INGREDIENTS: POLYGLYCERYL-6 DISTEARATE; PROPANEDIOL; ISODODECANE; CITRIC ACID MONOHYDRATE; GLYCERYL ISOSTEARATE; DIMETHICONE; WATER; SUNFLOWER OIL; XANTHAN GUM; ETHYLHEXYLGLYCERIN; BUTYL ACRYLATE/METHYL METHACRYLATE/METHACRYLIC ACID COPOLYMER (18000 MW); PHENOXYETHANOL; SODIUM LAURETH SULFATE; PONGAMIA PINNATA SEED; CASTOR OIL; BUTYLOCTYL SALICYLATE; POLYHYDROXYSTEARIC ACID (2300 MW); GLYCERIN; POLYGLYCERYL-10 DIPALMITATE; MEDIUM-CHAIN TRIGLYCERIDES; DIMETHICONE CROSSPOLYMER

DCL Non-nano Mineral Sunscreen SPF30